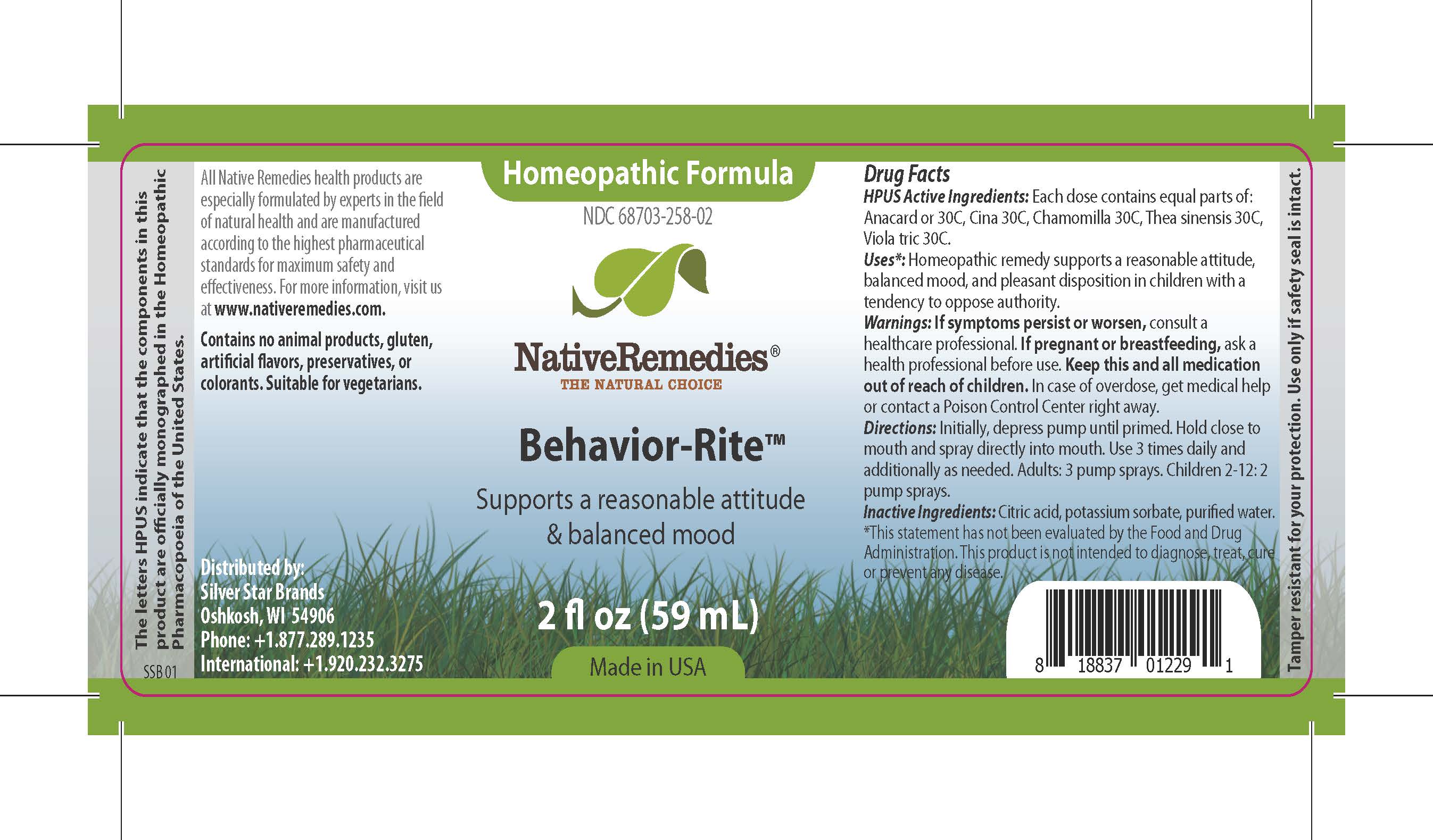 DRUG LABEL: Behavior-Rite
NDC: 68703-258 | Form: SPRAY
Manufacturer: Silver Star Brands
Category: homeopathic | Type: HUMAN OTC DRUG LABEL
Date: 20200221

ACTIVE INGREDIENTS: ARTEMISIA CINA FLOWER 30 [hp_C]/59 mL; SEMECARPUS ANACARDIUM JUICE 30 [hp_C]/59 mL; MATRICARIA RECUTITA 30 [hp_C]/59 mL; VIOLA TRICOLOR 30 [hp_C]/59 mL; CAMELLIA SINENSIS FLOWER 30 [hp_C]/59 mL
INACTIVE INGREDIENTS: POTASSIUM SORBATE; ANHYDROUS CITRIC ACID; WATER

NativeRemedies® Behavior-Rite™

HPUS Active Ingredients

Each dose contains equal parts of: Anacard or 30C, Cina 30C, Chamomilla 30C, Thea sinensis 30C, Viola tric 30C.

Uses

*Homeopathic remedy supports a reasonable attitude, balanced mood, and pleasant disposition in children with a tendency to oppose authority.

*This statement has not been evaluated by the Food and Drug Administration. This product is not intended to diagnose, treat, cure or prevent any disease.

Warnings

If symptoms persist or worsen, consult a healthcare professional. If pregnant or breastfeeding, ask a health professional before use. Keep this and all medication out of reach of children. In case of overdose, get medical help or contact a Poison Control Center right away.

Directions

Initially, depress pump until primed. Hold close to mouth and spray directly into mouth. Use 3 times daily and additionally as needed. Adults: 3 pump sprays. Children 2-12: 2 pump sprays.

Other Information

All Native Remedies health products are especially formulated by experts in the field of natural health and are manufactured according to the highest pharmaceutical standards for maximum safety and effectiveness. For more information, visit us at www.nativeremedies.com.

Contains no animal products, gluten, artifical flavors, preservatives, or colorants. Suitable for vegetarians.

Inactive Ingredients

Citric acid, potassium sorbate, purified water.

KEEP OUT OF REACH OF CHILDREN

Keep this and all medication out of reach of children.

PREGNANCY OR BREAST FEEDING

If pregnant or breastfeeding, ask a health professional before use.

PURPOSE

Supports a reasonable attitude & balanced mood